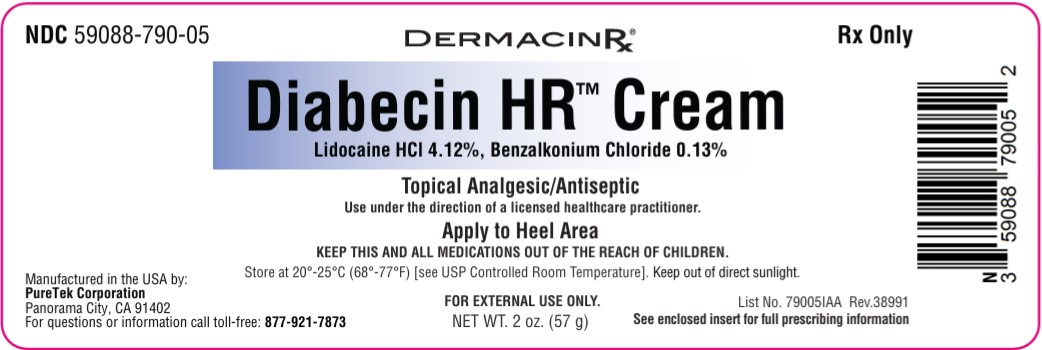 DRUG LABEL: Diabecin HR
NDC: 59088-790 | Form: CREAM
Manufacturer: PureTek Corporation
Category: prescription | Type: HUMAN PRESCRIPTION DRUG LABEL
Date: 20250610

ACTIVE INGREDIENTS: DIMETHICONE 50 mg/1 g; LIDOCAINE HYDROCHLORIDE 41.2 mg/1 g; BENZALKONIUM CHLORIDE 1.3 mg/1 g
INACTIVE INGREDIENTS: 1-O-(DIHYDROXYMETHYLSILYL)-.BETA.-D-MANNOPYRANURONIC ACID; PANTHENOL; PEUCEDANUM OSTRUTHIUM LEAF; SODIUM LAUROYL SARCOSINATE; BUTYROSPERMUM PARKII (SHEA) BUTTER; CALENDULA OFFICINALIS FLOWER; CETYL ALCOHOL; PHENOXYETHANOL; RETINYL PALMITATE; STEARIC ACID; TETRAHEXYLDECYL ASCORBATE; VITIS VINIFERA (GRAPE) SEED EXTRACT; TRIETHANOLAMINE; XANTHAN GUM; CHAMOMILE; GLYCERYL STEARATE; CARBOMER; CYCLOPENTASILOXANE; EDETATE DISODIUM; .ALPHA.-TOCOPHEROL ACETATE, DL-; PEG-100 STEARATE; POLYACRYLAMIDE (1500 MW); ZEA MAYS (CORN) STARCH; GLYCERIN; ALOE VERA LEAF JUICE; WATER; ARNICA MONTANA FLOWER; HELIANTHUS ANNUUS (SUNFLOWER) SEED OIL

NDC 59088-790 Diabecin HR

Full Prescribing Information: Description:

Diabecin HR™ Cream contains 41.2 mg of Lidocaine HCl per gram, and 1.3 mg of Benzalkonium Chloride per gram in a vehicle of Aloe Barbadensis (Aloe Vera) Leaf Juice Powder, Aqua (Purified Water), Arnica Montana Flower Extract, Butyrospermum Parkii (Shea) Butter, Calendula Officinalis Flower Extract, Carbomer, Cetyl Alcohol, Chamomilla Recutita (Matricaria) Flower Extract, Cyclopentasiloxane, Dimethicone, Disodium EDTA, DL-alpha Tocopheryl Acetate, GenRx® Complex (Proprietary Blend), Glycerin, Glyceryl Acrylate/Acrylic Acid Copolymer, Glyceryl Stearate, Helianthus Annuus (Sunflower) Seed Oil, Methylsilanol Mannuronate, Panthenol, PEG-100 Stearate, Peucedanum Ostruthium (Masterwort) Leaf Extract, Phenoxyethanol, Propylene Glycol, Retinyl Palmitate, Sodium Lauroyl Sarcosinate, Stearic Acid, Tetrahexyldecyl Ascorbate, Triethanolamine, Vitis Vinifera (Grape) Seed Extract, Xanthan Gum, Zea Mays (Corn) Starch.

INDICATIONS:

Diabecin HR™ Cream is indicated for the temporary relief of pain and itching associated with minor skin irritations. It combines the anesthetic properties of Lidocaine, and the antiseptic effects of Benzalkonium Chloride to provide effective care for damaged skin.

CLINICAL PHARMACOLOGY:

Pharmacodynamics

Lidocaine- is a common local anesthetic that relieves itching, burning, and pain. Topically, it blocks both initiation and conduction or nerve impulses by decreasing ionic flux through the neuronal membrane. Since it penetrates the skin, it creates an anesthetic effect by not just preventing pain signals from propagating to the brain out by stopping them before they begin. Benzalkonium Chloride serves as an antiseptic, preventing infection in minor skin injuries.

Pharmacokinetics

Absorption:

Lidocaine- Lidocaine may be absorbed following topical administration to mucous membranes, its rate and extent of absorption depending upon the specific site of application, duration of exposure, concentration and total dosage. In general, the rate of absorption of local anesthetic agents following topical application occurs most rapidly after intratracheal administration. Lidocaine is also well-absorbed from the gastrointestinal tract, but little intact drug appears in the circulation because of biotransformation in the liver. Lidocaine is metabolized rapidly by the liver and metabolites and unchanged drug are excreted by the kidneys. Biotransformation includes oxidative N-dealkylation, ring hydroxylation, cleavage of the amide linkage and conjugation. N-dealkylation, a major pathway of biotransformation, yields the metabolites monoethylglycinexylidide and glycinexylidide. The pharmacological/ toxicological actions of these metabolites are similar to, but less potent than, those of lidocaine. Approximately 90% of lidocaine administered is excreted in the form of various metabolites and less than 10% is excreted unchanged. The primary metabolite in urine is a conjugate of 4-hydroxy-2, 6-dimethylaniline. The plasma binding of lidocaine is dependent on drug concentration and the fraction bound decreases with increasing concentration. At concentrations of 1 to 4 g of free base per mL, 60 to 80 percent of lidocaine is protein bound. Binding is also dependent on the plasma concentration of the alpha-1-acid glycoprotein. Lidocaine crosses the blood-brain and placental barriers, presumably by passive diffusion. Studies of lidocaine metabolism following intravenous bolus injections have shown that the elimination half-life of this agent is typically 1.5 to 2 hours. Because of the rapid rate at which lidocaine is metabolized, any condition that affects liver function may alter lidocaine kinetics. The half-life may be prolonged two-fold or more in patients with liver dysfunction. Renal dysfunction does not affect lidocaine kinetics but may increase the accumulation of metabolites. Factors such as acidosis and the use of CNS stimulants and depressants affect the CNS levels of lidocaine required to produce overt systemic effects. Objective adverse manifestations become increasingly apparent with increasing venous plasma levels above 6 g free base per mL. In the rhesus monkey, arterial blood levels of 18-21 g/mL have been shown to be threshold for convulsive activity.

Benzalkonium Chloride acts locally with minimal systemic absorption.

Excretion:

Lidocaine- Lidocaine and its metabolites are excreted by the kidneys. Less than 10% of Lidocaine is excreted unchanged. The half-life of lidocaine elimination from the plasma following IV administration is 81 to 149 minutes (mean 107 ± 22 SD, n = 15). The systemic clearance is 0.33 to 0.90 L/min (mean 0.64 ± 0.18 SD, n = 15).

Benzalkonium chloride, a quaternary ammonium compound, is also minimally absorbed through the skin when applied topically. If some systemic absorption occurs, benzalkonium chloride is metabolized in the liver and the metabolites are primarily excreted via the kidneys into the urine. The small amount absorbed is eliminated relatively quickly, reducing the potential for systemic toxicity.

CONTRAINDICATIONS:

Tuberculosis or fungal lesions of the skin vaccinia, varicella and acute herpes simplex and in persons who have shown hypersensitivity to any of its components. Lidocaine is contraindicated in patients with a known history of hypersensitivity to local anesthetics of the amide type.

WARNINGS: For external use only. Not for ophthalmic use.

EXCESSIVE DOSING:
Excessive dosing by applying Diabecin HR™ Cream to larger areas or for longer than the recommended wearing time could result in increased absorption of lidocaine and high blood concentrations, leading to serious adverse effects (see ADVERSE REACTIONS, Systemic Reactions). Lidocaine toxicity could be expected at lidocaine blood concentrations above 5 mcg/mL. The blood concentration of lidocaine is determined by the rate of systemic absorption and elimination. Longer duration of application, application of more than the recommended number of patches, smaller patients, or impaired elimination may all contribute to increasing the blood concentration of lidocaine. With recommended dosing, the average peak blood concentration is about 0.13 mcg/ mL, but concentrations higher than 0.25 mcg/mL have been observed in some individuals.

PRECAUTIONS:

Allergic Reactions: Patients allergic to para-aminobenzoic acid derivatives (procaine, tetracaine, benzocaine, etc.) have not shown cross sensitivity to lidocaine. However, Diabecin HR™ Cream should be used with caution in patients with a history of drug sensitivities, especially if the etiologic agent is uncertain.

Non-intact Skin: Application to broken or inflamed skin, although not tested, may result in higher blood concentrations of lidocaine from increased absorption. Diabecin HR™ Cream is only recommended for use on intact skin.

External Heat Sources: Placement of external heat sources, such as heating pads or electric blankets, over Diabecin HR™ Cream is not recommended as this has not been evaluated and may increase plasma lidocaine levels.

Eye Exposure: The contact of Diabecin HR™ Cream with eyes, although not studied, should be avoided based on the f indings of severe eye irritation with the use of similar products in animals. If eye contact occurs, immediately wash out the eye with water or saline and protect the eye until sensation returns.

Drug Interactions

Antiarrhythmic Drugs: Diabecin HR™ Cream should be used with caution in patients receiving Class I antiarrhythmic drugs (such as tocainide and mexiletine) since the toxic effects are additive and potentially synergistic.

Local Anesthetics: When Diabecin HR™ Cream is used concomitantly with other products containing local anesthetic agents, the amount absorbed from all formulations must be considered.

Carcinogenesis, Mutagenesis, Impairment of Fertility

Carcinogenesis: A minor metabolite, 2,6-xylidine, has been found to be carcinogenic in rats. The blood concentration of this metabolite is negligible following application of lidocaine.

Mutagenesis: Lidocaine HCl is not mutagenic in Salmonella/mammalian microsome test nor clastogenic in chromosome aberration assay with human lymphocytes and mouse micronucleus test.

Impairment of Fertility: The effect of lidocaine on fertility has not been studied.

Pregnancy

Teratogenic Effects: Pregnancy Category B. Lidocaine has not been studied in pregnancy. Reproduction studies with lidocaine have been performed in rats at doses up to 30 mg/kg subcutaneously and have revealed no evidence of harm to the fetus due to lidocaine. There are, however, no adequate and well- controlled studies in pregnant women. Because animal reproduction studies are not always predictive of human response, lidocaine should be used during pregnancy only if clearly needed.

Labor and Delivery: Lidocaine has not been studied in labor and delivery. Lidocaine is not contraindicated in labor and delivery. Should lidocaine be used concomitantly with other products containing lidocaine, total doses contributed by all formulations must be considered.

NURSING MOTHERS

Nursing Mothers: Lidocaine has not been studied in nursing mothers. Lidocaine is excreted in human milk, and the milk: plasma ratio of lidocaine is 0.4. Caution should be exercised when lidocaine is administered to a nursing woman.

Pediatric Use: Safety and effectiveness in pediatric patients have not been established.

ADVERSE REACTIONS:

Application Site Reactions

Even though adverse reactions are rare, a very small percentage of patients experience an unpleasant burning sensation, redness, warmth, or stinging. It is advisable to apply a small amount on the forearm prior to first use. If any of these effects persist or worsen, contact your physician or pharmacist immediately. Systemic absorption of this medication is expected to be minimal when used as directed. However, if serious side effects occur (e.g., rash, swelling, severe dizziness), discontinue use and consult your pharmacist or physician. This is not a complete list of all possible side effects. You may report side effects to the FDA at 800-FDA-1088 or at http://www.fda.gov/medwatch.

Allergic Reactions:

Allergic and anaphylactoid reactions associated with lidocaine, although rare, can occur. They are characterized by angioedema, bronchospasm, dermatitis, dyspnea, hypersensitivity, laryngospasm, pruritus, shock, and urticaria. If they occur, they should be managed by conventional means. The detection of sensitivity by skin testing is of doubtful value.

Other Adverse Events:

Due to the nature and limitation of spontaneous reports in post marketing surveillance, causality has not been established for additional reported adverse events including: Asthenia, confusion, disorientation, dizziness, headache, hyperesthesia, hypoesthesia, lightheadedness, metallic taste, nausea, nervousness, pain exacerbated, paresthesia, somnolence, taste alteration, vomiting, visual disturbances such as blurred vision, flushing, tinnitus, and tremor.

Systemic (Dose-Related) Reactions:

Systemic adverse reactions following appropriate use of lidocaine is unlikely, due to the small dose absorbed (see CLINICAL PHARMACOLOGY, Pharmacokinetics). Systemic adverse effects of lidocaine are similar in nature to those observed with other amide local anesthetic agents, including CNS excitation and/or depression (light-headedness, nervousness, apprehension, euphoria, confusion, dizziness, drowsiness, tinnitus, blurred or double vision, vomiting, sensations of heat, cold or numbness, twitching, tremors, convulsions, unconsciousness, respiratory depression and arrest). Excitatory CNS reactions may be brief or not occur at all, in which case the first manifestation may be drowsiness merging into unconsciousness. Cardiovascular manifestations may include bradycardia, hypotension and cardiovascular collapse leading to arrest.

To report SUSPECTED ADVERSE REACTIONS, contact Actavis at 1-800- 272-5525 or FDA at 1-800-FDA-1088 or www.fda.gov/medwatch for voluntary reporting of adverse reactions.

OVERDOSAGE:

Lidocaine overdose from cutaneous absorption is rare but could occur. If there is any suspicion of lidocaine overdose (see ADVERSE REACTIONS, Systemic Reactions), drug blood concentration should be checked. The management of overdose includes close monitoring, supportive care, and symptomatic treatment. Dialysis is of negligible value in the treatment of acute overdose with lidocaine.

In the absence of massive topical overdose or oral ingestion, evaluation of symptoms of toxicity should include consideration of other etiologies for the clinical effects, or over dosage from other sources of lidocaine or other local anesthetics. The oral LD50 of lidocaine HCl is 459 (346 to 773) mg/kg (as the salt) in non-fasted female rats and 214 (159 to 324) mg/kg (as the salt) in fasted female rats, which are equivalent to roughly 4000 mg and 2000 mg, respectively, in a 60 to 70 kg man based on the equivalent surface area dosage conversion factors between species.

DOSAGE AND ADMINISTRATION:

Apply to the affected area of the heel two or three times daily or as directed by a licensed healthcare practitioner.

Use under the direction of a licensed healthcare practitioner.

HOW SUPPLIED:

Diabecin HR™ Cream is supplied in a 2 oz (57 g) tube (NDC 59088-790-05).

CAUTION: KEEP THIS AND ALL MEDICATIONS OUT OF THE REACH OF CHILDREN

Store at 20° to 25°C (68° to 77°F) [See USP Controlled Room Temperature].

Diabecin HR™ Cream

Manufactured by:

PureTek Corporation

Panorama City, CA 91402

For questions or information

call toll-free: 877-921-7873